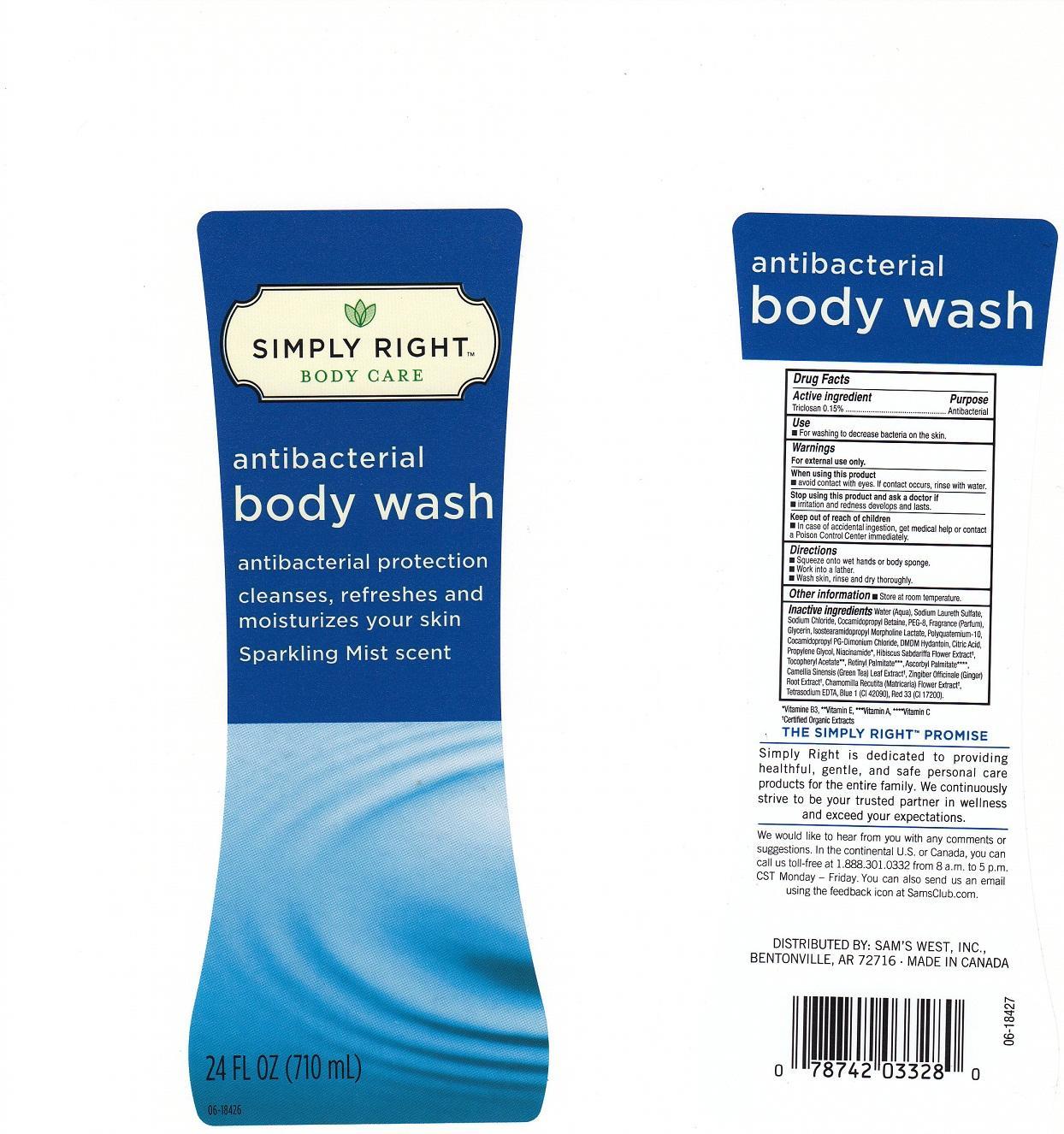 DRUG LABEL: SIMPLY RIGHT BODY CARE
NDC: 68196-809 | Form: LIQUID
Manufacturer: SAM'S WEST INC.
Category: otc | Type: HUMAN OTC DRUG LABEL
Date: 20130814

ACTIVE INGREDIENTS: TRICLOSAN 1.5 mg/1 mL
INACTIVE INGREDIENTS: WATER; SODIUM LAURETH SULFATE; SODIUM CHLORIDE; COCAMIDOPROPYL BETAINE; POLYETHYLENE GLYCOL 400; GLYCERIN; ISOSTEARAMIDOPROPYL MORPHOLINE LACTATE; POLYQUATERNIUM-10 (400 CPS AT 2%); COCAMIDOPROPYL PG-DIMONIUM CHLORIDE; DMDM HYDANTOIN; CITRIC ACID MONOHYDRATE; PROPYLENE GLYCOL; NIACINAMIDE; HIBISCUS SABDARIFFA FLOWER; .ALPHA.-TOCOPHEROL ACETATE; VITAMIN A PALMITATE; ASCORBYL PALMITATE; GREEN TEA LEAF; GINGER; CHAMOMILE; EDETATE SODIUM; FD&C BLUE NO. 1; D&C RED NO. 33

DRUG FACTS

ACTIVE INGREDIENT

TRICLOSAN 0.15%

PURPOSE

ANTIBACTERIAL

USE

FOR WASHING TO DECREASE BACTERIA ON THE SKIN.

WARNINGS

FOR EXTERNAL USE ONLY.

WHEN USING THIS PRODUCT

AVOID CONTACT WITH EYES. IF CONTACT OCCURS, RINSE WITH WATER.

STOP USING THIS PRODUCT AND ASK A DOCTOR IF

IRRITATION AND REDNESS DEVELOPS AND LASTS.

KEEP OUT OF REACH OF CHILDREN

IN CASE OF ACCIDENTAL INGESTION, GET MEDICAL HELP OR CONTACT A POISON CONTROL CENTER IMMEDIATELY.

DIRECTIONS

SQUEEZE ONTO WET HANDS OR BODY SPONGE. WORK INTO A LATHER. WASH SKIN, RINSE AND DRY THOROUGHLY.

OTHER INFORMATION

STORE AT ROOM TEMPERATURE.

INACTIVE INGREDIENTS:

WATER (AQUA), SODIUM LAURETH SULFATE, SODIUM CHLORIDE, COCAMIDOPROPYL BETAINE, PEG-8, FRAGRANCE (PARFUM), GLYCERIN, ISOSTEARAMIDOPROPYL MORPHOLINE LACTATE, POLYQUATERNIUM-10, COCAMIDOPROPYL PG-DIMONIUM CHLORIDE, DMDM HYDANTOIN, CITRIC ACID, PROPYLENE GLYCOL, NIACINAMIDE, HIBISCUS SABDARIFFA FLOWER EXTRACT, TOCOPHERYL ACETATE, RETINYL PALMITATE, ASCORBYL PALMITATE, CAMELLIA SINENSIS (GREEN TEA) LEAF EXTRACT, ZINGIBER OFFICINALE (GINGER) ROOT EXTRACT, CHAMOMILLA RECUTITA (MATRICARIA) FLOWER EXTRACT, TETRASODIUM EDTA, BLUE 1 (CI 42090), RED 33 (CI 17200).